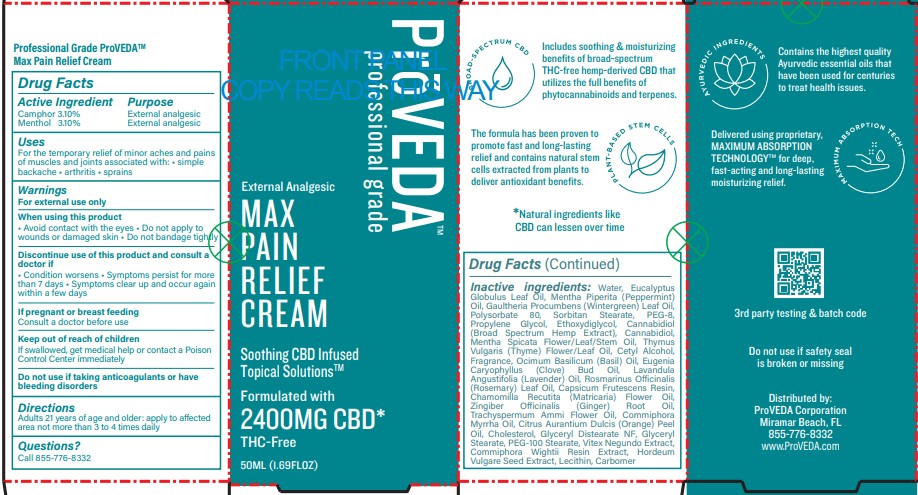 DRUG LABEL: MAX PAIN RELIEF
NDC: 82707-101 | Form: CREAM
Manufacturer: PROVEDA
Category: otc | Type: HUMAN OTC DRUG LABEL
Date: 20230926

ACTIVE INGREDIENTS: MENTHOL 3.1 g/100 mL; CAMPHOR OIL 3.1 g/100 mL
INACTIVE INGREDIENTS: HEMP; THYME OIL; CAPSICUM FRUTESCENS WHOLE; GLYCERYL DISTEARATE; CETYL ALCOHOL; GLYCERYL MONOSTEARATE; PEG-100 STEARATE; GINGER OIL; MYRRH OIL; VITEX NEGUNDO WHOLE; HORDEUM VULGARE WHOLE; PEPPERMINT OIL; PROPYLENE GLYCOL; CLOVE OIL; ROSEMARY OIL; CHAMOMILE FLOWER OIL; GAULTHERIA PROCUMBENS WHOLE; POLYSORBATE 80; POLYETHYLENE GLYCOL 400; COMMIPHORA WIGHTII RESIN; CARBOMER 940; LECITHIN, SOYBEAN; EUCALYPTUS OIL; PEG-6 SORBITAN STEARATE; DIETHYLENE GLYCOL MONOETHYL ETHER; MENTHA SPICATA OIL; BASIL OIL; WATER; CANNABIS SATIVA WHOLE; LAVENDER OIL; TRACHYSPERMUM AMMI FLOWER; ORANGE PEEL; CHOLESTEROL

PROVEDA - MAX PAIN RELIEF CREAM (82707-101)

ACTIVE INGREDIENTS

CAMPHOR 3.10%

MENTHOL 3.10%

PURPOSE

EXTERNAL ANALGESIC

USES

FOR THE TEMPORARY RELIEF OF MINOR ACHES AND PAINS OF MUSCLES AND JOINTS ASSOCIATED WITH:

- SIMPLE BACKACHE
- ARTHRITIS
- SPRAINS

WARNINGS

FOR EXTERNAL USE ONLY.

WHEN USING THIS PRODUCT

- AVOID CONTACT WITH THE EYES
- DO NOT APPLY TO WOUNDS OR DAMAGED SKIN
- DO NOT BANDAGE TIGHTLY

DISCONTINUE USE OF THIS PRODUCY AND CONSULT A DOCTOR IF

- CONDITION WORSENS
- SYMPTOMS PERSIST FOR MORE THAN 7 DAYS
- SYMPTOMS CLEAR UP AND OCCUR AGAIN WITHIN A FEW DAYS

IF PREGNANT OR BREAST FEEDING

- CONSULT A DOCTOR BEFORE USE

DO NOT USE IF TAKING ANTICOAGULANTS OR HAVE BLEEDING DISORDERS.

KEEP OUT OF REACH OF CHILDREN.

IF SWALLOWED, GET MEDICAL HELP OR CONTACT A POISON CONTROL CENTER IMMEDIATELY.

DIRECTIONS

ADULTS 21 YEARS OF AGE AND OLDER: APPLY TO AFFECTED AREA NOT MORE THAN 3 TO 4 TIMES DAILY.

QUESTIONS?

CALL 855-776-8332

INACTIVE INGREDIENTS

WATER, EUCALYPTUS GLOBULUS LEAF OIL, MENTHA PIPERITA (PEPPERMINT) OIL, GAULTHERIA PROCUMBENS (WINTERGREEN) LEAF OIL, POLYSORBATE 80, SORBITAN STEARATE, PEG-8, PROPYLENE GLYCOL, ETHOXYDIGLYCOL, CANNABIDIOL (BROAD SPECTRUM HEMP EXTRACT), CANNABIDIOL, MENTHA SPICATA FLOWER/LEAF/STEM OIL, THYMUS VULGARIS (THYME) FLOWER/LEAF OIL, CETYL ALCOHOL, FRAGRANCE, OCIMUM BASILICUM (BASIL) OIL, EUGENIA CARYOPHYLLUS (CLOVE) BUD OIL, LAVANDULA ANGUSTIFOLIA (LAVENDER) OIL, ROSMARINUS OFFICINALIS (ROSEMARY) LEAF OIL, CAPSICUM FRUTESCENS RESIN, CHAMOMILLA RECUTITA (MATRICARIA) FLOWER OIL, ZINGIBER OFFICINALIS (GINGER) ROOT OIL, TRACHYSPERMUM AMMI FLOWER OIL, COMMIPHORA MYRRHA OIL, CITRUS AURANTIUM DULCIS (ORANGE) PEEL OIL, CHOLESTEROL, GLYCERYL DISTEARATE NF, GLYCERYL STEARATE, PEG-100 STEARATE, VITEX NEGUNDO EXTRACT, COMMIPHORA WIGHTII RESIN EXTRACT, HORDEUM VULGARE SEED EXTRACT, LECITHIN, CARBOMER